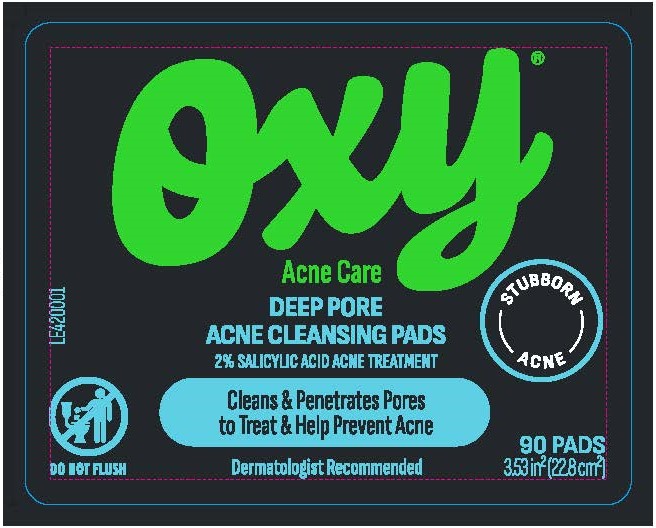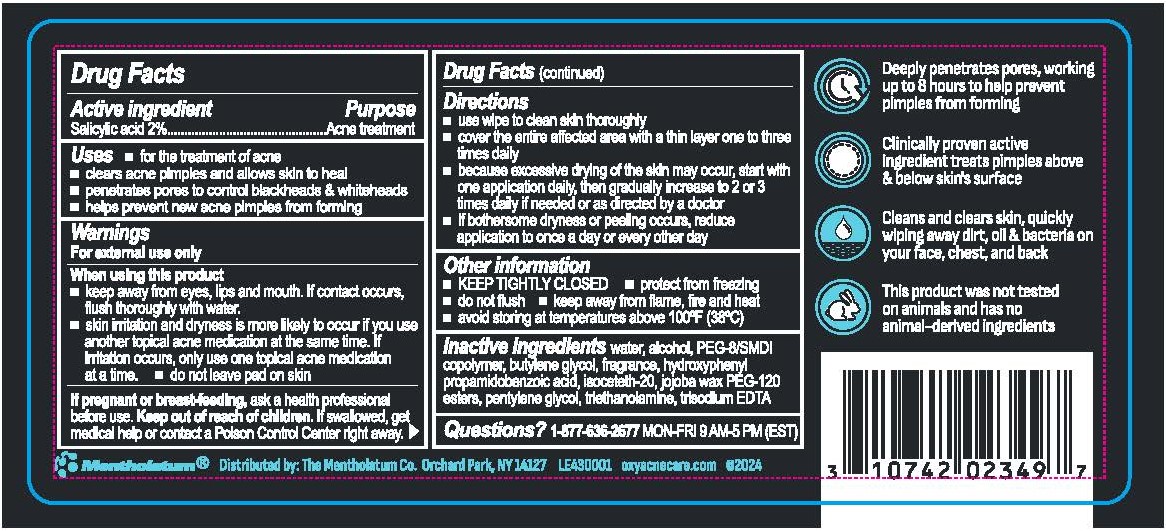 DRUG LABEL: Oxy Deep Pore Acne Cleansing Pads
NDC: 10742-1006 | Form: CLOTH
Manufacturer: The Mentholatum Company
Category: otc | Type: HUMAN OTC DRUG LABEL
Date: 20241226

ACTIVE INGREDIENTS: SALICYLIC ACID 20 mg/1 1
INACTIVE INGREDIENTS: WATER; SIMMONDSIA CHINENSIS (JOJOBA) SEED WAX; BUTYLENE GLYCOL; FRAGRANCE 13576; TRISODIUM EDTA; PEG-8/SMDI COPOLYMER; PENTYLENE GLYCOL; TRIETHANOLAMINE; ISOCETETH-20; ALCOHOL; HYDROXYPHENYL PROPAMIDOBENZOIC ACID

Drug Facts - Oxy Deep Pore Acne Cleansing Pads

Active ingredient

Salicylic acid 2%

Purpose

Acne treatment

Uses

- for the treatment of acne
- clears acne pimples and allows skin to heal
- penetrates pores to control blackheads & whiteheads
- helps prevent new acne pimples from forming

Warnings

For external use only

When using this product

- keep away from eyes, lips and mouth. If contact occurs, flush thoroughly with water.
- skin irritation and dryness is more likely to occur if you use another topical acne medication at the same time. If irritation occurs, only use one topical acne medication at a time.
- do not leave pad on skin

If pregnant or breast feeding,

ask a health professional before use.

Keep out of reach of children

If swallowed, get medical help or contact a Poison Control Center right away.

Directions

- use wipe to clean skin thoroughly
- cover the entire affected area with a thin layer one to three times daily
- because excessive drying of the skin may occur, start with one application daily, then gradually increase to 2 or 3 times daily if needed or as directed by a doctor
- if bothersome dryness or peeling occurs, reduce application to once a day or every other day

Inactive ingredients

water, alcohol, PEG-8/SMDI copolymer, butylene glycol, fragrance, hydroxyphenyl propamidobenzoic acid, isoceteth-20, jojoba wax PEG-120 esters, pentylene glycol, triethanolamine, trisodium EDTA

Questions?

1-877-636-2677 MON-FRI 9AM-5PM (EST)